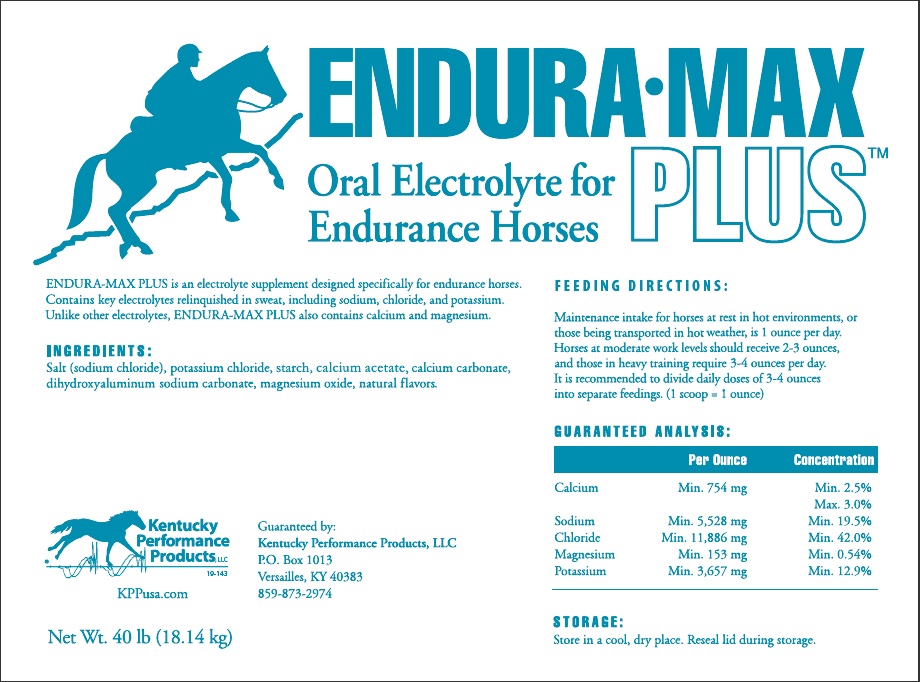 DRUG LABEL: ENDURA MAX
NDC: 86105-674 | Form: POWDER
Manufacturer: Kentucky Performance Products
Category: animal | Type: OTC ANIMAL DRUG LABEL
Date: 20190506

ACTIVE INGREDIENTS: DIHYDROXYALUMINUM SODIUM CARBONATE .05 kg/1 kg
INACTIVE INGREDIENTS: SODIUM CHLORIDE; POTASSIUM CHLORIDE; STARCH, CORN; CALCIUM ACETATE; CALCIUM CARBONATE; SODIUM CARBONATE; MAGNESIUM OXIDE

DESCRIPTION

ENDURA-MAX PLUS™

Oral Electrolytes for Endurance Horses

ENDURA-MAX PLUS is an electrolyte supplement designed specifically for endurance horses. Contains key electrolytes relinguished in sweat, including sodium, chloride and potassium. Unlike other electrolytes, ENDURA-MAX PLUS also provides calcium and magnesium.

INGREDIENTS:

Salt (sodium chloride), potassium chloride, starch, calcium acetate, calcium carbonate, dihydroxyaluminum sodium carbonate, magnesium oxide, natural flavors.

DOSAGE AND ADMINISTRATION

FEEDING DIRECTIONS:

Maintenance intake for horses at rest in hot environments, or those being transported in hot weather, is 1 ounce per day. Horses at moderate work levels should receive 2-3 ounces per day, and those in heavy training require 3-4 ounces per day. It is recommended to divide daily doses of 3-4 ounces into separate feedings. (1 scoop = 1 ounce)

GUARANTEED ANALYSIS:

 | Per Ounce | Concentration
Calcium | Min. 754 mg | Min. 2.5%; Max. 3.0%
Sodium | Min. 5,528 mg | Min. 19.5%
Chloride | Min. 11,886 mg | Min. 42.0%
Magnesium | Min. 153 mg | Min. 0.54%
Potassium | Min. 3,657 mg | Min. 12.9%

STORAGE AND HANDLING

Store in a cool, dry place. Reseal lid during storage.

Principal Dsiplay Panel - 40 pound (18.14 kg) Pail

ENDURA-MAX PLUS™

Oral Electrolytes for Endurance Horses